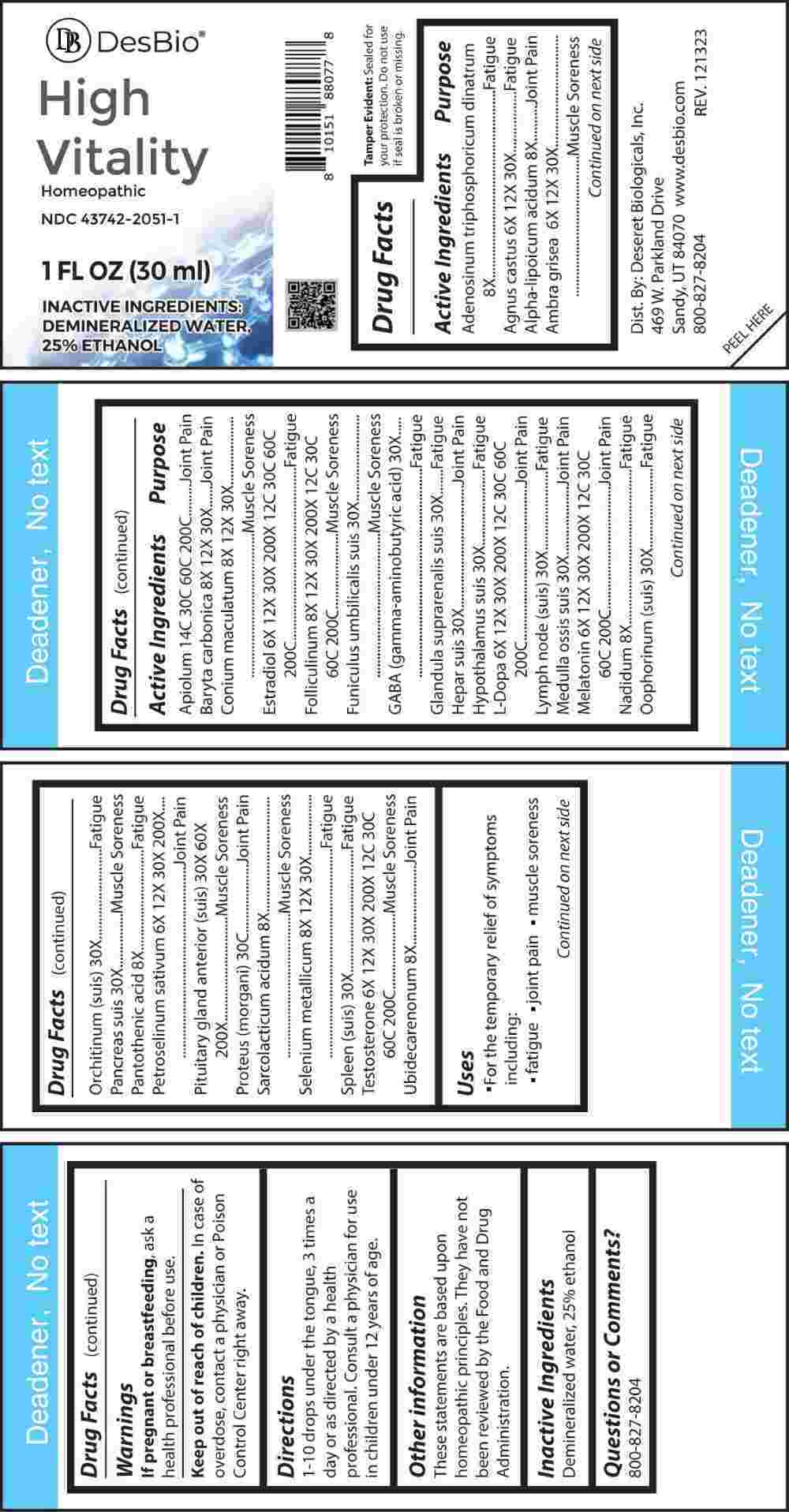 DRUG LABEL: High Vitality
NDC: 43742-2051 | Form: LIQUID
Manufacturer: Deseret Biologicals, Inc.
Category: homeopathic | Type: HUMAN OTC DRUG LABEL
Date: 20240313
DEA Schedule: CIII

ACTIVE INGREDIENTS: CHASTE TREE FRUIT 6 [hp_X]/1 mL; AMBERGRIS 6 [hp_X]/1 mL; PETROSELINUM CRISPUM WHOLE 6 [hp_X]/1 mL; ESTRADIOL 6 [hp_X]/1 mL; LEVODOPA 6 [hp_X]/1 mL; MELATONIN 6 [hp_X]/1 mL; TESTOSTERONE 6 [hp_X]/1 mL; ADENOSINE TRIPHOSPHATE DISODIUM 8 [hp_X]/1 mL; ALPHA LIPOIC ACID 8 [hp_X]/1 mL; NADIDE 8 [hp_X]/1 mL; PANTOTHENIC ACID 8 [hp_X]/1 mL; LACTIC ACID, L- 8 [hp_X]/1 mL; UBIDECARENONE 8 [hp_X]/1 mL; BARIUM CARBONATE 8 [hp_X]/1 mL; CONIUM MACULATUM FLOWERING TOP 8 [hp_X]/1 mL; SELENIUM 8 [hp_X]/1 mL; ESTRONE 8 [hp_X]/1 mL; SUS SCROFA UMBILICAL CORD 30 [hp_X]/1 mL; .GAMMA.-AMINOBUTYRIC ACID 30 [hp_X]/1 mL; SUS SCROFA ADRENAL GLAND 30 [hp_X]/1 mL; PORK LIVER 30 [hp_X]/1 mL; SUS SCROFA HYPOTHALAMUS 30 [hp_X]/1 mL; SUS SCROFA LYMPH 30 [hp_X]/1 mL; SUS SCROFA BONE MARROW 30 [hp_X]/1 mL; SUS SCROFA OVARY 30 [hp_X]/1 mL; SUS SCROFA TESTICLE 30 [hp_X]/1 mL; SUS SCROFA PANCREAS 30 [hp_X]/1 mL; SUS SCROFA SPLEEN 30 [hp_X]/1 mL; SUS SCROFA PITUITARY GLAND 30 [hp_X]/1 mL; APIOLE (PARSLEY) 14 [hp_C]/1 mL; PROTEUS MORGANII 30 [hp_C]/1 mL
INACTIVE INGREDIENTS: WATER; ALCOHOL

DRUG FACTS:

ACTIVE INGREDIENTS:

Adenosinum Triphosphoricum Dinatrum 8X, Agnus Castus 6X, 12X, 30X, Alpha-Lipoicum Acidum 8X, Ambra Grisea 6X, 12X, 30X, Apiolum 14C, 30C, 60C, 200C, Baryta Carbonica 8X, 12X, 30X, Conium Maculatum 8X, 12X, 30X, Estradiol 6X, 12X, 30X, 200X, 12C, 30C, 60C, 200C, Folliculinum 8X, 12X, 30X, 200X, 12C, 30C, 60C, 200C, Funiculus Umbilicalis Suis 30X, Gaba (Gamma-aminobutyric Acid) 30X, Glandula Suprarenalis Suis 30X, Hepar Suis 30X, Hypothalamus Suis 30X, L-Dopa 6X, 12X, 30X, 200X, 12C, 30C, 60C, 200C, Lymph Node (Suis) 30X, Medulla Ossis Suis 30X, Melatonin 6X, 12X, 30X, 200X, 12C, 30C, 60C, 200C, Nadidum 8X, Oophorinum (Suis) 30X, Orchitinum (Suis) 30X, Pancreas Suis 30X, Pantothenic Acid 8X, Petroselinum Sativum 6X, 12X, 30X, 200X, Pituitary Gland Anterior (Suis) 30X, 60X, 200X, Proteus (Morgani) 30C, Sarcolacticum Acidum 8X, Selenium Metallicum 8X, 12X, 30X, Spleen (Suis) 30X, Testosterone 6X, 12X, 30X, 200X, 12C, 30C, 60C, 200C, Ubidecarenonum 8X.

PURPOSE:

Adenosinum Triphosphoricum Dinatrum - Fatigue, Agnus Castus - Fatigue, Alpha-Lipoicum Acidum – Joint Pain, Ambra Grisea – Muscle Soreness, Apiolum – Joint Pain, Baryta Carbonica – Joint Pain, Conium Maculatum – Muscle Soreness, Estradiol - Fatigue, Folliculinum – Muscle Soreness, Funiculus Umbilicalis Suis – Muscle Soreness, Gaba (Gamma-aminobutyric Acid) - Fatigue, Glandula Suprarenalis Suis - Fatigue, Hepar Suis – Joint Pain, Hypothalamus Suis - Fatigue, L-Dopa – Joint Pain, Lymph Node (Suis) - Fatigue, Medulla Ossis Suis – Joint Pain, Melatonin – Joint Pain, Nadidum - Fatigue, Oophorinum (Suis) - Fatigue, Orchitinum (Suis)- Fatigue, Pancreas Suis – Muscle Soreness, Pantothenic Acid - Fatigue, Petroselinum Sativum – Joint Pain, Pituitary Gland Anterior (Suis) – Muscle Soreness, Proteus (Morgani) – Joint Pain, Sarcolacticum Acidum – Muscle Soreness, Selenium Metallicum - Fatigue, Spleen (Suis) - Fatigue, Testosterone – Muscle Soreness, Ubidecarenonum – Joint Pain

USES:

• For the temporary relief of symptoms including:

• fatigue • joint pain • muscle soreness

These statements are based upon homeopathic principles. They have not been reviewed by the Food and Drug Administration.

WARNINGS:

If pregnant or breast-feeding, ask a health professional before use.

Keep out of reach of children. In case of overdose, contact a physician or Poison Control Center right away.

Tamper Evident: Sealed for your protection. Do not use if seal is broken or missing.

KEEP OUT OF REACH OF CHILDREN:

In case of overdose, contact a physician or Poison Control Center right away.

DIRECTIONS:

1-10 drops under the tongue, 3 times a day or as directed by a health professional. Consult a physician for use in children under 12 years of age.

INACTIVE INGREDIENTS:

Demineralized water, 25% ethanol

QUESTIONS:

Dist. By: Deseret Biologicals, Inc.

469 W. Parkland Drive

Sandy, UT 84070

www.desbio.com

800-827-8204

PACKAGE LABEL DISPLAY:

Des Bio

High Vitality

Homeopathic

NDC 43742-2051-1

1 FL OZ (30 ml)